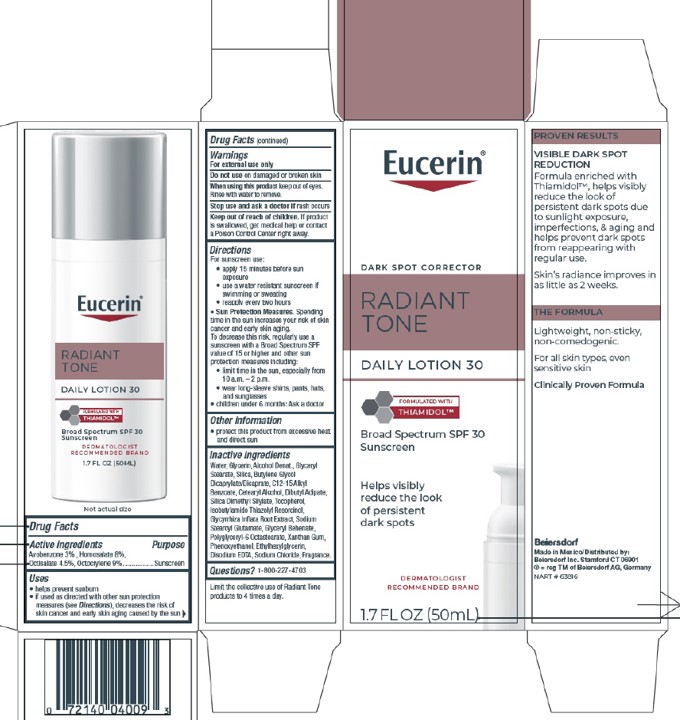 DRUG LABEL: Eucerin Radiant Tone
NDC: 10356-395 | Form: LOTION
Manufacturer: Beiersdorf Inc
Category: otc | Type: HUMAN OTC DRUG LABEL
Date: 20251216

ACTIVE INGREDIENTS: OCTOCRYLENE 9 g/100 g; HOMOSALATE 8 g/100 g; AVOBENZONE 3 g/100 g; OCTISALATE 4.5 g/100 g
INACTIVE INGREDIENTS: SODIUM CHLORIDE; ALCOHOL; ETHYLHEXYLGLYCERIN; EDETATE DISODIUM; SODIUM STEAROYL GLUTAMATE; GLYCERYL MONOSTEARATE; BUTYLENE GLYCOL DICAPRYLATE/DICAPRATE; GLYCYRRHIZA INFLATA ROOT; CETOSTEARYL ALCOHOL; TOCOPHEROL; WATER; GLYCERIN; SILICA DIMETHYL SILYLATE; PHENOXYETHANOL; XANTHAN GUM; SILICA; ISOBUTYLAMIDO THIAZOLYL RESORCINOL; GLYCERYL DIBEHENATE; DIBUTYL ADIPATE; C12-15 ALKYL BENZOATE

Eucerin Radiant Tone Lotion

Active ingredients

Avobenzone 3%

Homosalate 8%

Octisalate 4.5%

Octocrylene 9%

Purpose

Sunscreens

Uses
• helps prevent sunburn
• if used as directed with other sun protection measures (see Directions),
decreases the risk of skin cancer and early skin aging caused by the sun

Warnings
For external use only

.

Do not use on damaged or broken skin.

When using this product keep out of eyes. Rinse with water to remove.

Stop use and ask a doctor if rash occurs

Keep out of reach of children. If swallowed, get medical help or contact a Poison Control Center right away.

Directions

For sunscreen use:
• apply liberally 15 minutes before sun exposure
• use a water resistant sunscreen if swimming or sweating
• reapply at least every 2 hours
• children under 6 months of age: Ask a doctor
• Sun Protection Measures. Spending time in the sun increases your risk of skin cancer and
early skin aging. To decrease this risk, regularly use a sunscreen with a Broad Spectrum SPF
value of 15 or higher, and other sun protection measures including:
• limit time in the sun, especially from 10 a.m. - 2 p.m.
• wear long-sleeved shirts, pants, hats, and sunglasses.
• children under 6 months of age: Ask a doctor.

Other information

protect this product from excessive heat and direct sun

Inactive ingredients

Water, Glycerin, Alcohol Denat., Glyceryl
Stearate, Silica, Butylene Glycol
Dicaprylate/Dicaprate, C12-15 Alkyl
Benzoate, Cetearyl Alcohol, Dibutyl Adipate,
Silica Dimethyl Silylate, Tocopherol,
Isobutylamido Thiazolyl Resorcinol,
Glycyrrhiza Inflata Root Extract, Sodium
Stearoyl Glutamate, Glyceryl Behenate,
Polyglyceryl-6 Octastearate, Xanthan Gum,
Phenoxyethanol, Ethylhexylglycerin,
Disodium EDTA, Sodium Chloride, Fragrance.

PACKAGE LABEL

Eucerin

Dark Spot Corrector

Radiant Tone

Daily Lotion 30

Broad Spectrum SPF 30
Sunscreen

Formulated with Thiamidol

Helps visibly reduce the look of persistent dark spots

DERMATOLGIST RECOMMENDED BRAND

OL